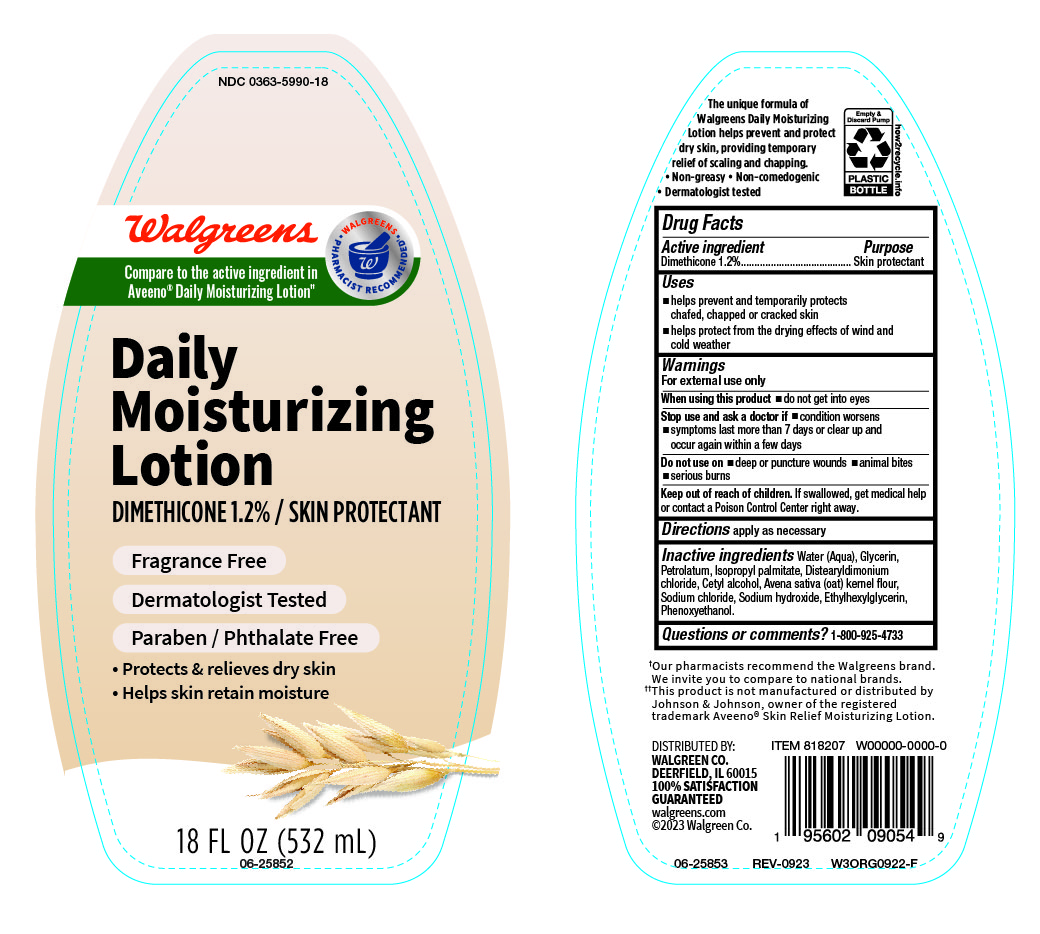 DRUG LABEL: Daily Moisturizer
NDC: 0363-5990 | Form: LOTION
Manufacturer: Walgreen
Category: otc | Type: HUMAN OTC DRUG LABEL
Date: 20240614

ACTIVE INGREDIENTS: DIMETHICONE 1200 mg/100 mL
INACTIVE INGREDIENTS: WATER; DISTEARYLDIMONIUM CHLORIDE; CETYL ALCOHOL; SODIUM CHLORIDE; ETHYLHEXYLGLYCERIN; GLYCERIN; ISOPROPYL PALMITATE; SODIUM HYDROXIDE; OATMEAL; PHENOXYETHANOL; PETROLATUM

Daily Moisturizing Lotion NDC 0363-5990-18

Active Ingredient

Dimethicone 1.2%

Purpose

Skin Protectant

Uses

- Helps prevent and temporarily protects chafed, chapped or cracked skin.
- Helps protect from the drying effects of winf and cold weather.

Warnings

For external use only

When using this product

- do not get into eyes

Stop use and ask a doctor if

- Condition worsens
- Symptoms last more than 7 days or clear up and occur again within a few days.

Do not use on

- deep or puncture wounds
- animal bites
- serious burns

Keep out of reach of children

If swallowed, get medical help or contact a Poison Control Center right away.

Directions

Apply as necessary

Inactive Ingredients

Water (Aqua), Glycerin, Petrolatum, Isopropyl Palmitate, Distearyldimonium Chloride, Cetyl Alcohol, Avena Sativa (Oat) Kernel Flour, Sodium Chloride, Sodium Hydroxide, Ethylhexylglycerin, Phenoxyethanol.

Questions or Comments ?

1-800-925-4733